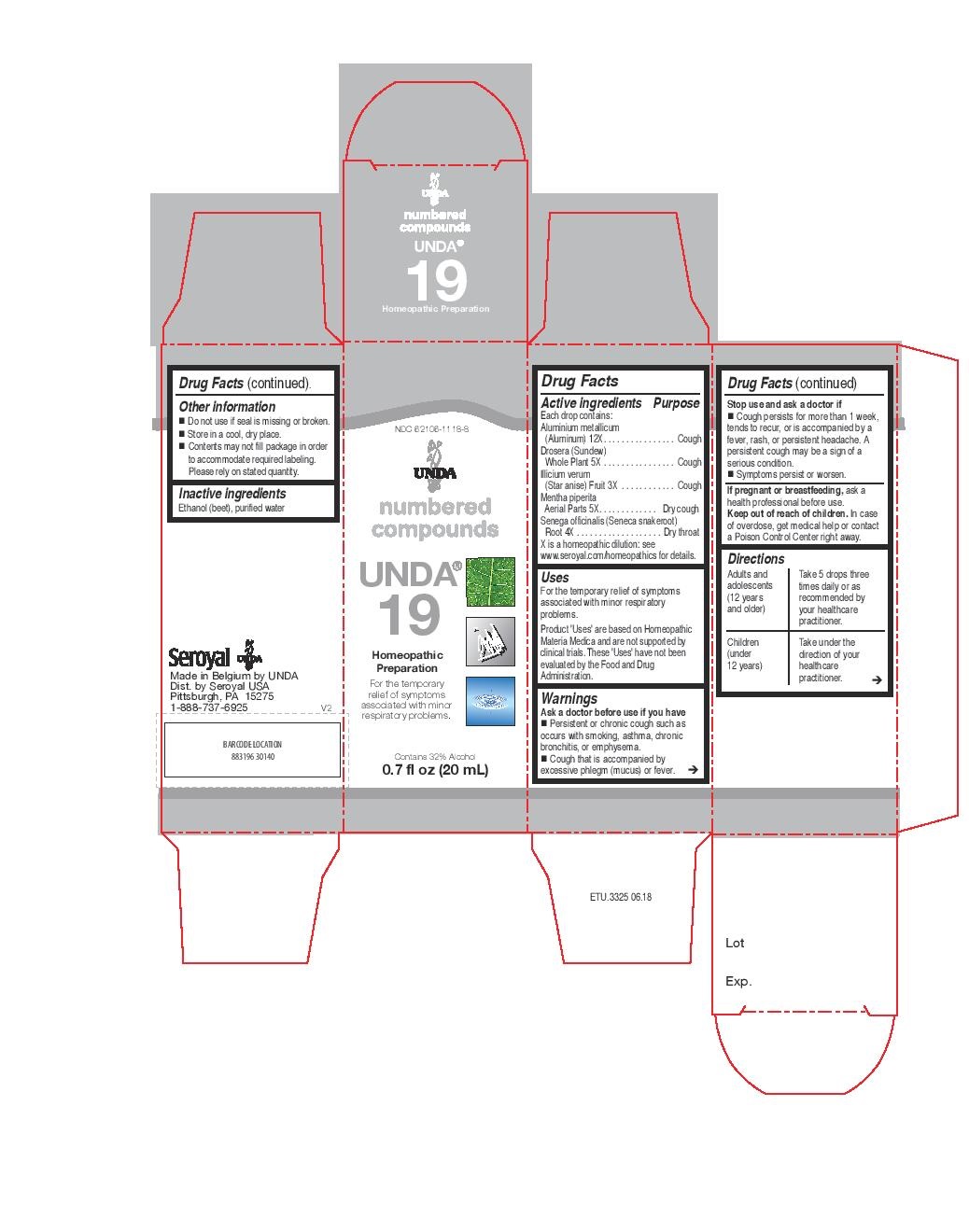 DRUG LABEL: UNDA 19
NDC: 62106-1118 | Form: LIQUID
Manufacturer: Seroyal USA
Category: homeopathic | Type: HUMAN OTC DRUG LABEL
Date: 20221109

ACTIVE INGREDIENTS: ALUMINUM 12 [hp_X]/20 mL; STAR ANISE FRUIT 3 [hp_X]/20 mL; POLYGALA SENEGA ROOT 4 [hp_X]/20 mL; DROSERA ROTUNDIFOLIA FLOWERING TOP 5 [hp_X]/20 mL; PEPPERMINT 5 [hp_X]/20 mL
INACTIVE INGREDIENTS: ALCOHOL; WATER

UNDA 19

Active ingredients
Each drop contains:
Aluminium metallicum (Aluminum) 12X
Drosera (Sundew) Whole Plant 5X
Illicium verum (Star anise) Fruit 3X
Mentha piperita Aerial Parts 5X
Senega officinalis (Seneca snakeroot) Root 4X

Uses
For the temporary relief of symptoms associated with minor respiratory problems.

Warnings
Ask a doctor before use if you have
Persistent or chronic cough such as
occurs with smoking, asthma, chronic
bronchitis, or emphysema.
Cough that is accompanied by
excessive phlegm (mucus) or fever.

Stop use and ask a doctor if
Cough persists for more than 1 week,
tends to recur, or is accompanied by a
fever, rash, or persistent headache. A
persistent cough may be a sign of a
serious condition.
Symptoms persist or worsen.
If pregnant or breastfeeding, ask a
health professional before use.
Keep out of reach of children. In case
of overdose, get medical help or contact
a Poison Control Center right away.

Keep out of reach of children. In case
of overdose, get medical help or contact
a Poison Control Center right away.

PREGNANCY OR BREAST FEEDING

If pregnant or breastfeeding, ask a
health professional before use.

Ask a doctor before use if you have
Persistent or chronic cough such as
occurs with smoking, asthma, chronic
bronchitis, or emphysema.
Cough that is accompanied by
excessive phlegm (mucus) or fever

Stop use and ask a doctor if
Cough persists for more than 1 week,
tends to recur, or is accompanied by a
fever, rash, or persistent headache. A
persistent cough may be a sign of a
serious condition.

Symptoms persist or worsen.

Other information
Do not use if seal is missing or broken.
Store in a cool, dry place.

Contents may not fill package in order to accommodate required labeling. Please rely on stated quantity

Inactive ingredients
Ethanol (beet), purified water

Directions
Adults and adolescents (12 years and older)
Take 5 drops three times daily or as
recommended by your healthcare
practitioner.

Children (under 12 years)
Take under the direction of your
healthcare practitioner.

Uses
For the temporary relief of symptoms associated with minor respiratory problems.

Directions

Adults and adolescents (12 years and older)
Take 5 drops three times daily or as

recommended by your healthcare practitioner.

Children (under 12 years)

Take under the direction of your healthcare practitioner.

PACKAGE LABEL

NDC 62106-1118-8

UNDA

numbered compounds

UNDA 19

Homeopathic Preparation

For the temporary relief of symptoms

associated with minor respiratory problems.

Contains 32% Alcohol

0.7 fl oz (20 mL)